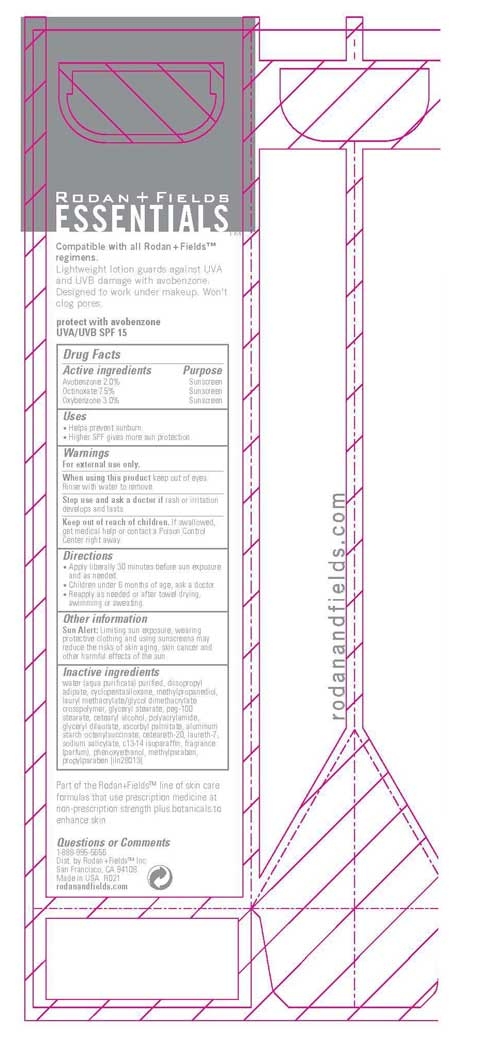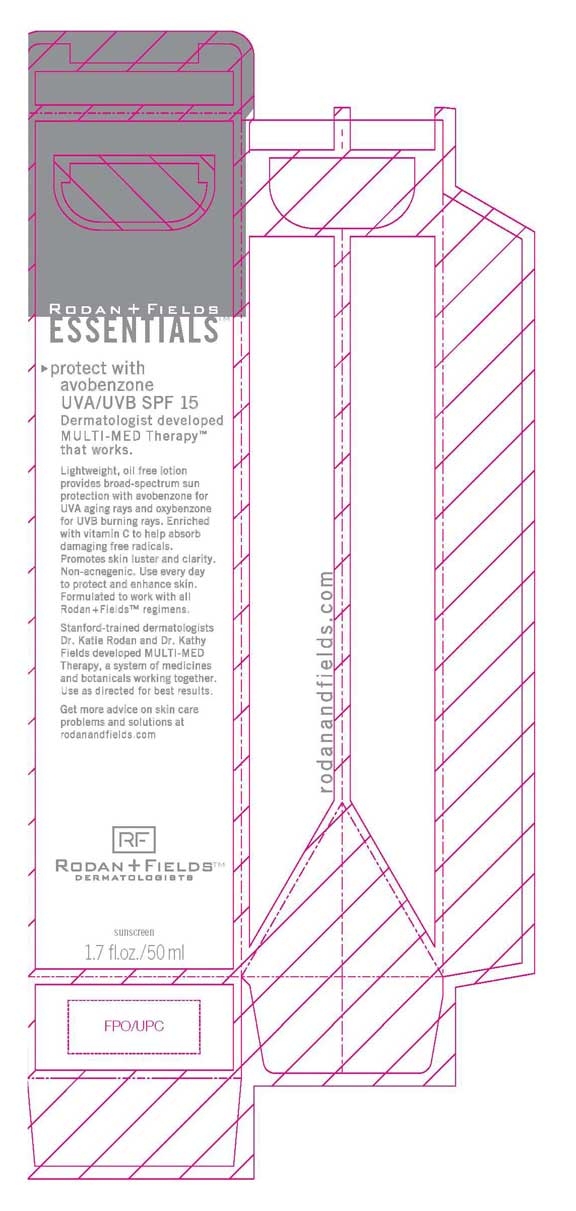 DRUG LABEL: Rodan and Fields
NDC: 56152-0815 | Form: CREAM
Manufacturer: Cosmetic Enterprises Ltd.
Category: otc | Type: HUMAN OTC DRUG LABEL
Date: 20110328

ACTIVE INGREDIENTS: AVOBENZONE 2.0 mL/100 mL; OCTINOXATE 7.5 mL/100 mL; OXYBENZONE 3.0 mL/100 mL
INACTIVE INGREDIENTS: DIISOPROPYL ADIPATE; CYCLOMETHICONE 5; METHYLPROPANEDIOL; GLYCERYL MONOSTEARATE; PEG-100 STEARATE; CETOSTEARYL ALCOHOL; ASCORBYL PALMITATE; ALUMINUM STARCH OCTENYLSUCCINATE; POLYOXYL 20 CETOSTEARYL ETHER; LAURETH-7; SODIUM SALICYLATE; C13-14 ISOPARAFFIN; PHENOXYETHANOL; METHYLPARABEN; PROPYLPARABEN

Essentials UVA/UVB SPF 15

Active Ingredients Purpose

Avobenzone 2.0% Sunscreen

Octinoxate 7.5% Sunscreen

Oxybenzone 3.0 % Sunscreen

Warnings

For external use only.

When using this product keep out of eyes. Rinse with water to remove.

Stop use and ask a doctor if rash or irritation develops and lasts

Keep out of of children. If swallowed, get medical help or contact a Poison Control Center right away.

INACTIVE INGREDIENT

water (aqua purificata) purified, diisopropyl adipate, cyclopentasiloxane, methylpropanediol, lauryl methacrylate/glycol dimethacrylate crosspolymer, glyceryl stearate, peg-100 stearate, cetearyl alcohol, polyacrylamide, glyceryl dilaurate, ascorbyl palmitate, aluminum starch octenylsuccinate, ceteareth-20, laureth-7, sodium salicylate, c13-14 isoparaffin, fragrance (parfum), phenoxyethanol, methylparaben, propylparaben

Questions or Comments

1-888-895-5656

GENERAL PRECAUTIONS

Sun Alert: Limiting sun exposure, wearing protective clothing, and using sunscreens may reduce the risks of skin aging, skin cancer and other harmful effects of the sun.

PACKAGE LABEL

Essential UVA/UVB SPF 15

1.7 fl.oz./50 ml